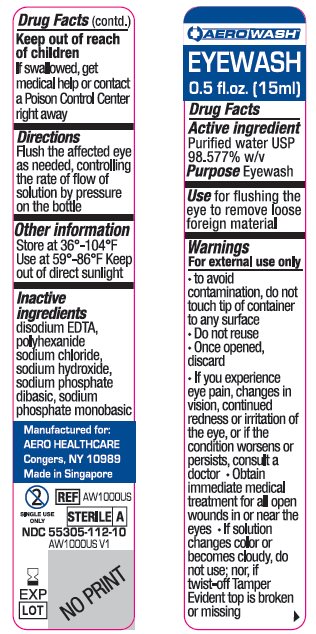 DRUG LABEL: Aerowash Eyewash and Skin-Rinse
NDC: 55305-112 | Form: SOLUTION
Manufacturer: Aero Healthcare
Category: otc | Type: HUMAN OTC DRUG LABEL
Date: 20180607

ACTIVE INGREDIENTS: WATER 98.577 mL/100 mL
INACTIVE INGREDIENTS: POLIHEXANIDE; EDETATE DISODIUM; SODIUM HYDROXIDE; SODIUM PHOSPHATE, DIBASIC, DODECAHYDRATE; SODIUM PHOSPHATE, MONOBASIC, DIHYDRATE; SODIUM CHLORIDE

AEROWASH EYEWASH

Active ingredient

Purified water USP

98.577% w/v

Purpose

Eyewash

Use

Use for flushing the eye to remove loose foreign material.

Warnings

For External Use Only

To avoid contamination, do not touch tip of container to any surface.

Do not reuse.

Once opened, discard.

If you experience eye pain, changes in vision, continued redness or irritation of the eye, or if the condition worsens or persists, consult a doctor.

Obtain immediate medical treatment for all open wounds in or near the eyes.

If solution changes color or becomes cloudy do not use nor, if twist-off Tamper Evident top is broken or missing.

Keep out of reach of children

If swallowed, get medical help or contact a Poison Control Center right away.

Directions

Flush the affected eye as needed, controlling the rate of flow of solution by pressure on the bottle.

Other Information

Store at 36°-104°F

Use at 59°-86°F

Keep out of direct sunlight

Inactive ingredients

disodium EDTA
polyhexanide
sodium chloride
sodium hydroxide
sodium phosphate, dibasic
sodium phosphate, monobasic

Manufactured for:

Aero Healthcare

Congers, NY 10989

Made in Singapore